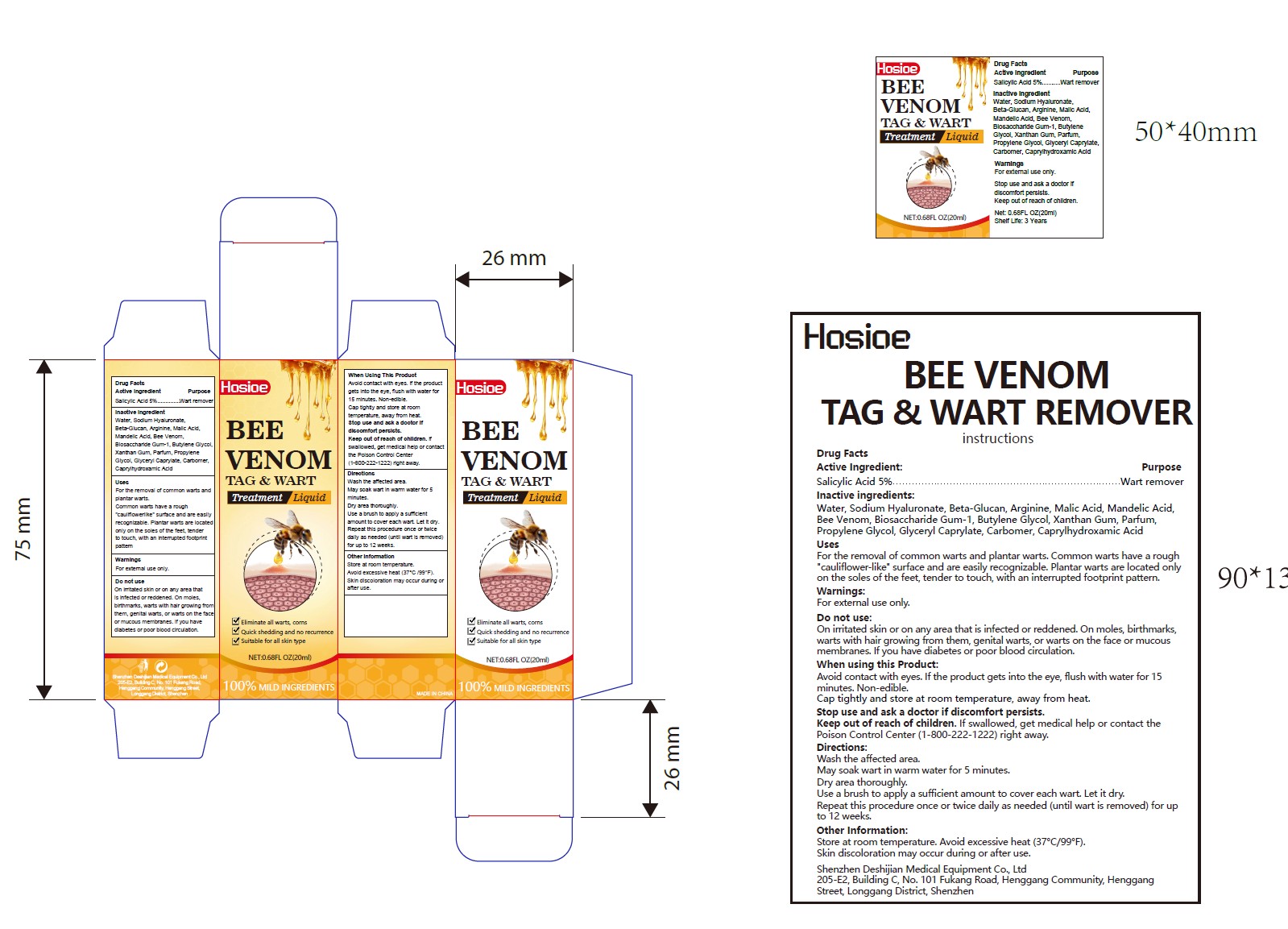 DRUG LABEL: BEE VENOM TAG   WART REMOVER
NDC: 85741-002 | Form: CREAM
Manufacturer: Shenzhen Deshijian Medical Equipment Co., Ltd
Category: otc | Type: HUMAN OTC DRUG LABEL
Date: 20250705

ACTIVE INGREDIENTS: SALICYLIC ACID 5 g/100 mL
INACTIVE INGREDIENTS: ARGININE; BIOSACCHARIDE GUM-1; GLYCERYL CAPRYLATE; CARBOMER; CAPRYLHYDROXAMIC ACID; PARFUMIDINE; BUTYLENE GLYCOL; PROPYLENE GLYCOL; WATER; SODIUM HYALURONATE; MALIC ACID; APIS MELLIFERA VENOM; MANDELIC ACID; XANTHAN GUM; 1,3-BETA-GLUCAN SYNTHASE COMPONENT FKS1

ACTIVE INGREDIENT

Salicylic Acid 5% Wart remover

INACTIVE INGREDIENT

Water, Sodium Hyaluronate, Beta-Glucan, Arginine, Malic Acid, Mandelic Acid,
Bee Venom, Biosaccharide Gum-1, Butylene Glycol, Xanthan Gum, Parfum,
Propylene Glycol, Glyceryl Caprylate, Carbomer, Caprylhydroxamic Acid

PURPOSE

Eliminate all warts, cornsyQuick shedding and no recurrenceySuitable for all skin type

Keep out of reach of children. If swallowed, get medical help or contact the
Poison Control Center (1-800-222-1222) right away.

DOSAGE AND ADMINISTRATION

For the removal of common warts and plantar warts. Common warts have a rough
"cauliflower-like" surface and are easily recognizable. Plantar warts are located only
on the soles of the feet, tender to touch, with an interrupted footprint pattern

INDICATIONS AND USAGE

Directions:Wash the affected area.May soak wart in warm water for 5 minutes.Dry area thoroughly.Use a brush to apply a sufficient amount to cover each wart. Let it dry.Repeat this procedure once or twice daily as needed (until wart is removed) for upto 12 weeks.

WARNINGS

For external use only. Flammable. Keep away from fire and flame

STOP USE

On irritated skin or on any area that is infected or reddened. On moles, birthmarks,
warts with hair growing from them, genital warts, or warts on the face or mucous
membranes. If you have diabetes or poor blood circulation.

OTHER SAFETY INFORMATION

Store at room temperature. Avoid excessive heat (37°C/99°F).
Skin discoloration may occur during or after use